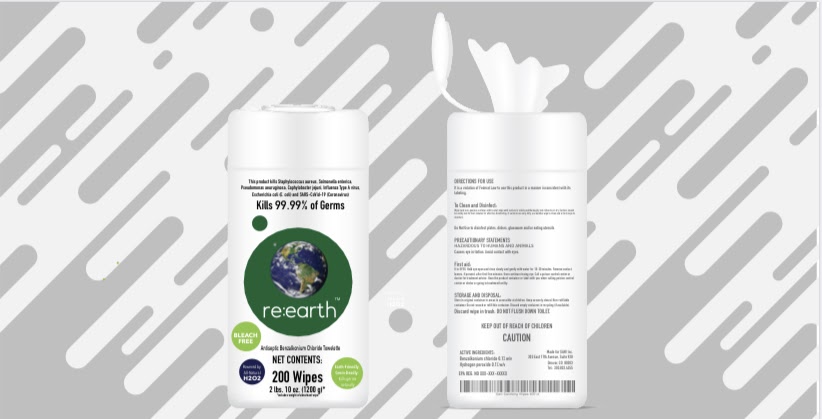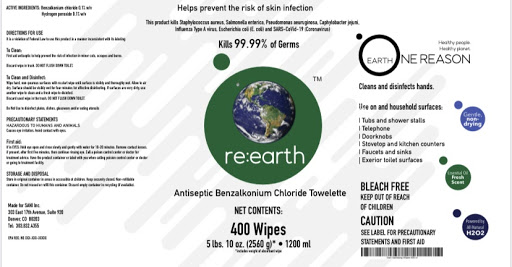 DRUG LABEL: reEarth Hand Sanitizer wipe
NDC: 77368-011 | Form: CLOTH
Manufacturer: NuGenTec
Category: otc | Type: HUMAN OTC DRUG LABEL
Date: 20201014

ACTIVE INGREDIENTS: BENZALKONIUM CHLORIDE 6.8 mg/100 mL
INACTIVE INGREDIENTS: GLYCERIN 1.45 mL/100 mL; HYDROGEN PEROXIDE 0.1 mL/100 mL; WATER

re:earth wipe Hand Sanitizer

Active Ingredient(s)

Benzalkonium Chloride 0.13%

Purpose

Antiseptic, Hand Sanitizer, Antibacterial

Use

Hand Sanitizer wipe to help reduce bacteria that potentially can cause disease. For use when soap and water are not available.

Warnings

For external use only. Flammable. Keep away from heat or flame

Do not use

- in children less than 2 months of age
- on open skin wounds

When using this product keep out of eyes, ears, and mouth. In case of contact with eyes, rinse eyes thoroughly with water.
Stop use and ask a doctor if irritation or rash occurs. These may be signs of a serious condition.
Keep out of reach of children. If swallowed, get medical help or contact a Poison Control Center right away.

Stop use and ask a doctor if irritation or rash occurs. These may be signs of a serious condition.

Keep out of reach of children. If swallowed, get medical help or contact a Poison Control Center right away.

Directions

- Wet hands thoroughly with the product to cover all surfaces. Allow to dry without wiping.
- Supervise children under 6 years of age when using this product to avoid swallowing.

Other information

- Store between 0-40C (32-104F)
- Avoid freezing and excessive heat above 40C (104F)

Inactive ingredients

glycerin, hydrogen peroxide, purified water USP

Package Label - Principal Display Panel

160 in Canister NDC: 77368-011-20